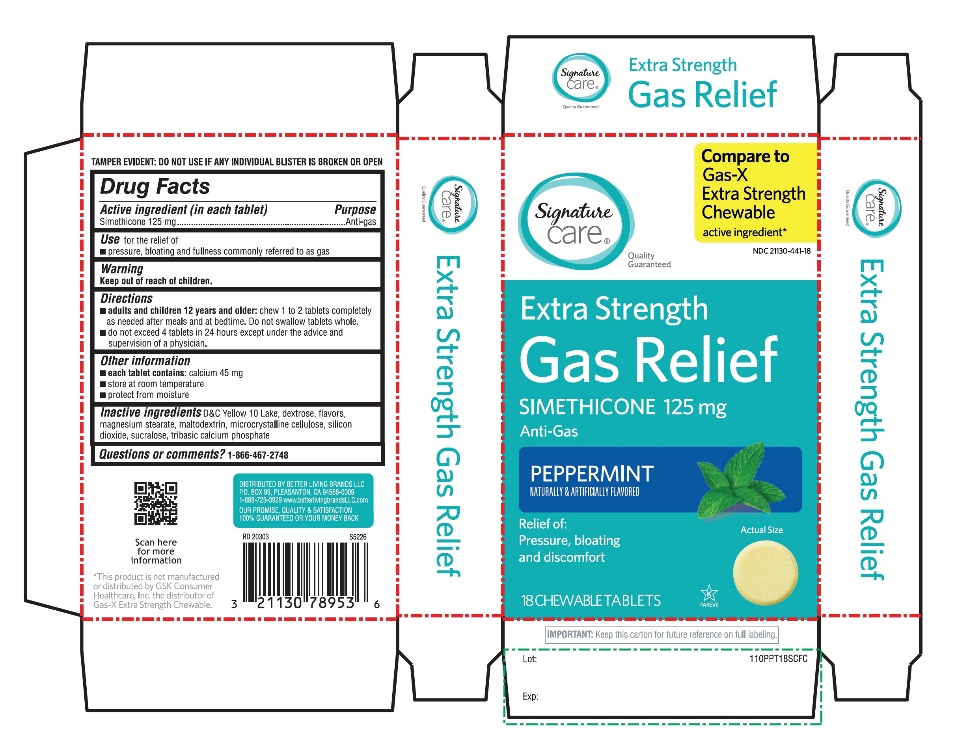 DRUG LABEL: Extra Strength Gas Relief
NDC: 21130-441 | Form: TABLET, CHEWABLE
Manufacturer: SAFEWAY
Category: otc | Type: HUMAN OTC DRUG LABEL
Date: 20251029

ACTIVE INGREDIENTS: DIMETHICONE, UNSPECIFIED 125 mg/1 1
INACTIVE INGREDIENTS: D&C YELLOW NO. 10; DEXTROSE, UNSPECIFIED FORM; MAGNESIUM STEARATE; MALTODEXTRIN; MICROCRYSTALLINE CELLULOSE; SILICON DIOXIDE; SUCRALOSE; TRIBASIC CALCIUM PHOSPHATE

Extra Strength Gas Relief Tablets

Active Ingredient (in each tablet)

Simethicone 125 mg

PURPOSE

Anti-gas

USE(S)

relieves:

- Pressure, bloating and fullness commonly referred to as gas

Keep out of reach of children

In case of overdose, get medical help or contact a poison control center immediately.

Directions

- adults and Childrens 12 years and older:chew 1 to 2 tablets thoroughly as needed after meals and at bedtime
- do not exceed 4 tablets in a 24 hour period except under the advice and supervision of a physician

Other Information

- each tablet contains:calcium 45 mg
- store at room temperature
- protect from moisture

Inactive Ingredients

D&C red # 30 aluminum lake, D&C yellow # 10 aluminum lake, dextrose, flavor, magnesium stearate, maltodextrin, microcrystalline cellulose, sorbitol, sucrose

Principal Display Panel

*Compare to the active ingredient in Gas-X Extra Strength
NDC 21130-441-48
Extra strength
Gas Relief
Simethicone 125 mg/Anti-Gas
Fast Relief of Pressure, Bloating & Discomfort

Peppermint Flavor

Naturally and Artificially Flavored

18 Chewable Tablets

*This product is not manufactured or distributed by GSK Consumer Healthcare, the distributor of Gas-X Extra Strength.

IMPORTANT: Keep this carton for future reference on full labeling.